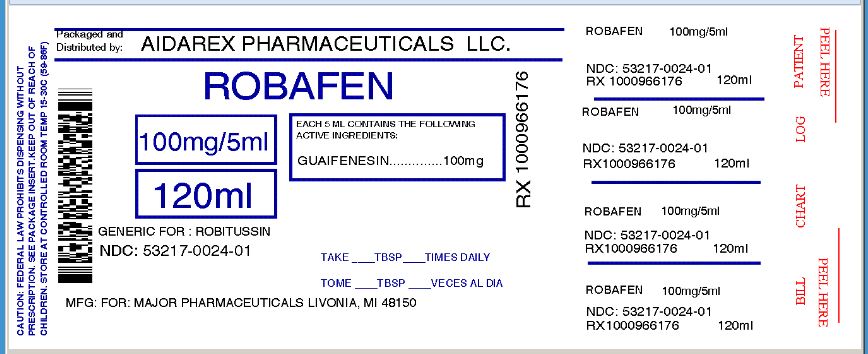 DRUG LABEL: ROBAFEN COUGH FORMULA
NDC: 53217-024 | Form: SYRUP
Manufacturer: Aidarex Pharmaceuticals LLC
Category: otc | Type: HUMAN OTC DRUG LABEL
Date: 20131003

ACTIVE INGREDIENTS: GUAIFENESIN 100 mg/5 mL
INACTIVE INGREDIENTS: PROPYLENE GLYCOL; SODIUM BENZOATE; SACCHARIN SODIUM; ANHYDROUS CITRIC ACID; GLYCERIN; MENTHOL; CORN SYRUP; WATER; CARAMEL; FD&C RED NO. 40

ROBAFEN™ COUGH FORMULA

Drug Facts

Active ingredient (in each teaspoonful (5 mL))

Guaifenesin USP 100 mg

Purpose

Expectorant

Uses

helps loosen phlegm (mucus) and thin bronchial secretions to make coughs more productive

Warnings

Ask a doctor before use if

- you have a cough that lasts or a chronic cough such as occurs with smoking, asthma, chronic bronchitis or emphysema
- cough occurs with too much phlegm (mucus)

Stop use and ask a doctor if cough lasts more than 7 days, comes back, or occurs with fever, rash, or headache that lasts. These could be signs of a serious condition.

PREGNANCY OR BREAST FEEDING

If pregnant or breast-feeding, ask a health professional before use.

KEEP OUT OF REACH OF CHILDREN

Keep out of the reach of children. In case of overdose, get medical help or contact a Poison Control Center right away.

Directions

do not take more than 6 doses in any 24 hour period

adults and children 12 years and over | 2 - 4 teaspoons every 4 hours or as directed by a doctor
children under 12 years | do not use

Other information

- each teaspoonful (5 mL) contains: sodium 3 mg
- store at room temperature 15°-30°C (59°-86°F)

Inactive ingredients

caramel powder, citric acid, corn syrup, FD&C Red #40, glycerin, menthol, propylene glycol, purified water, sodium benzoate, sodium saccharin

Questions?

Adverse Drug Event Call: (800) 616-2471

Distributed by
MAJOR PHARMACEUTICALS
31778 Enterprise Drive
Livonia, MI 48150 USA

Repackaged By :
Aidarex Pharmaceuticals LLC,
Corona, CA 92880

PRINCIPAL DISPLAY PANEL

NDC 53217-0024-01
TAMPER-EVIDENT

Robafen™
Syrup

(brand of Guaifenesin syrup USP
100 mg per 5 mL)

EXPECTORANT

Each teaspoonful (5 mL) contains:

Guaifenesin
(Glyceryl Guaiacolate), USP 100 mg

TAMPER-EVIDENT: Do not use this product
if inner foil seal over the mouth of the
bottle is cut, torn, broken or missing.

For Dispensing Purpose Only

Distributed by
MAJOR PHARMACEUTICALS
31778 Enterprise Drive
Livonia, MI 48150 USA

Repackaged By :
Aidarex Pharmaceuticals LLC,
Corona, CA 92880